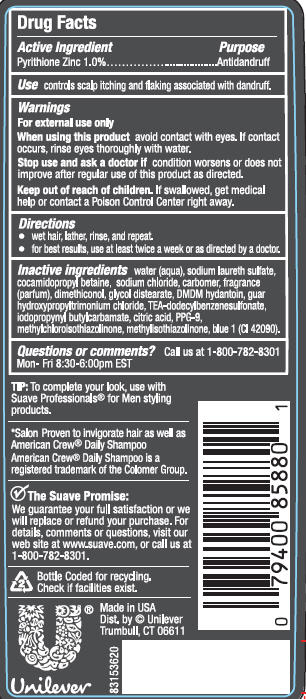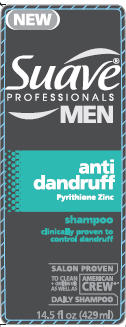 DRUG LABEL: Suave
NDC: 64942-1130 | Form: SHAMPOO
Manufacturer: Conopco Inc. d/b/a Unilever
Category: otc | Type: HUMAN OTC DRUG LABEL
Date: 20110407

ACTIVE INGREDIENTS: Pyrithione Zinc 1.0 mL/100 mL
INACTIVE INGREDIENTS: WATER; SODIUM LAURETH SULFATE; COCAMIDOPROPYL BETAINE; SODIUM CHLORIDE; CARBOMER HOMOPOLYMER TYPE C; GLYCOL STEARATE; DMDM HYDANTOIN; TEA-DODECYLBENZENESULFONATE; IODOPROPYNYL BUTYLCARBAMATE; CITRIC ACID MONOHYDRATE; PPG-9; METHYLCHLOROISOTHIAZOLINONE; METHYLISOTHIAZOLINONE; FD&C BLUE NO. 1; GUAR HYDROXYPROPYLTRIMONIUM CHLORIDE (1.7 SUBSTITUENTS PER SACCHARIDE)

Suave Professionals Men Anti Dandruff Shampoo PDP and drug facts box

Active Ingredient

Pyrithione Zinc (1.0%)

Purpose
Antidandruff

INDICATIONS AND USAGE

Use controls scalp itching and flaking associated with dandruff.

Warnings
For external use only

When using this product avoid contact with eyes. If contact occurs, rinse eyes thoroughly with water.

Stop use and ask a doctor if condition worsens or does not improve after regular use of this product as directed.

Keep out of reach of children. If swallowed, get medical help or contact a Poison Control Center right away.

Directions
· wet hair, lather, rinse, and repeat.
· for best results, use at least twice a week or as directed by a doctor.

Inactive Ingredients
Water
Sodium Laureth Sulfate
Cocamidopropyl Betaine
Sodium Chloride
Carbomer
Fragrance
Dimethiconol
Glycol Distearate
DMDM Hydantoin
Guar Hydroxypropyltrimonium Chloride
TEA-Dodecylbenzenesulfonate
Iodopropynyl Butylcarbamate
Citric Acid
PPG-9
Methylchloroisothiazolinone
Methylisothiazolinone
Blue 1 (CI 42090)

Questions/Comments?

call us at 1-800-782-8301 Mon - Fri 8:30 - 6:00 pm EST

PACKAGE LABEL

PDP back

PACKAGE LABEL

14.5 oz front